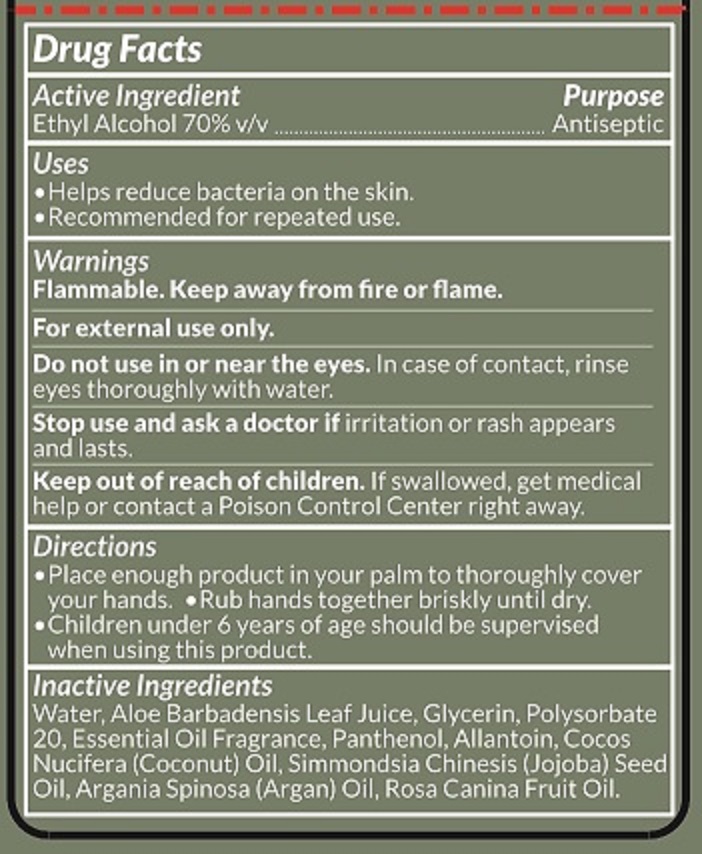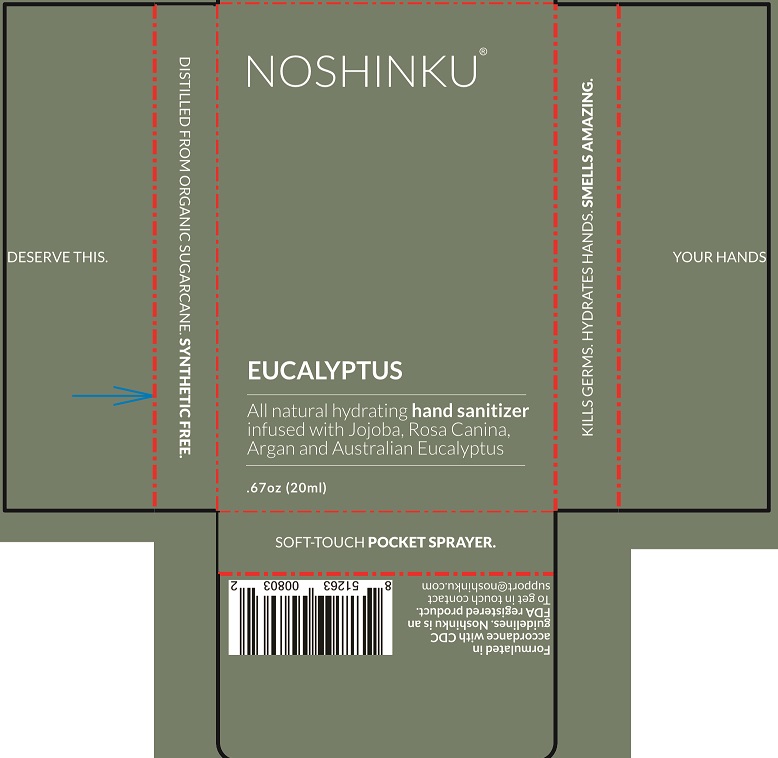 DRUG LABEL: Noshinku Eucalyptus Hand Sanitizer
NDC: 73898-002 | Form: SOLUTION
Manufacturer: Noshinku
Category: otc | Type: HUMAN OTC DRUG LABEL
Date: 20240514

ACTIVE INGREDIENTS: ALCOHOL 70 mL/100 mL
INACTIVE INGREDIENTS: ALOE VERA LEAF; GLYCERIN; POLYSORBATE 20; PANTHENOL; ALLANTOIN; COCONUT OIL; JOJOBA OIL; ARGAN OIL; ROSA CANINA FRUIT OIL; WATER

Noshinku Eucalyptus Hand Sanitizer (73898-002)

ACTIVE INGREDIENT

ETHYL ALCOHOL 70% V/V

PURPOSE

ANTISEPTIC

USES

- HELPS REDUCE BACTERIA ON THE SKIN.
- RECOMMENDED FOR REPEATED USE.

WARNINGS

FLAMMABLE. KEEP AWAY FROM FIRE OR FLAME.

FOR EXTERNAL USE ONLY.

DO NOT USE IN OR NEAR THE EYES. IN CASE OF CONTACT, RINSE EYES THOROUGHLY WITH WATER.

STOP USE AND CONSULT A DOCTOR IF IRRITATION OR RASH APPEARS AND LASTS.

KEEP OUT OF REACH OF CHILDREN. IF SWALLOWED, GET MEDICAL HELP OR CONTACT POISON CONTROL CENTER RIGHT AWAY.

DIRECTIONS

- PLACE ENOUGH PRODUCT IN YOUR PALM TO THOROUGHLY COVER YOUR HANDS.
- RUB HANDS TOGETHER BRISKLY UNTIL DRY.
- CHILDREN UNDER 6 YEARS OF AGE SHOULD BE SUPERVISED WHEN USING THIS PRODUCT.

INACTIVE INGREDIENTS

WATER, ALOE BARBADENSIS LEAF JUICE, GLYCERIN, POLYSORBATE 20, ESSENTIAL OIL FRAGRANCE, PANTHENOL, ALLANTOIN, COCOS NUCIDERA (COCONUT) OIL, SIMMONDSIA CHINENSIS (JOJOBA) OIL, ARGANIA SPINOSA (ARGAN) OIL, ROSA CANINA FRUIT OIL.